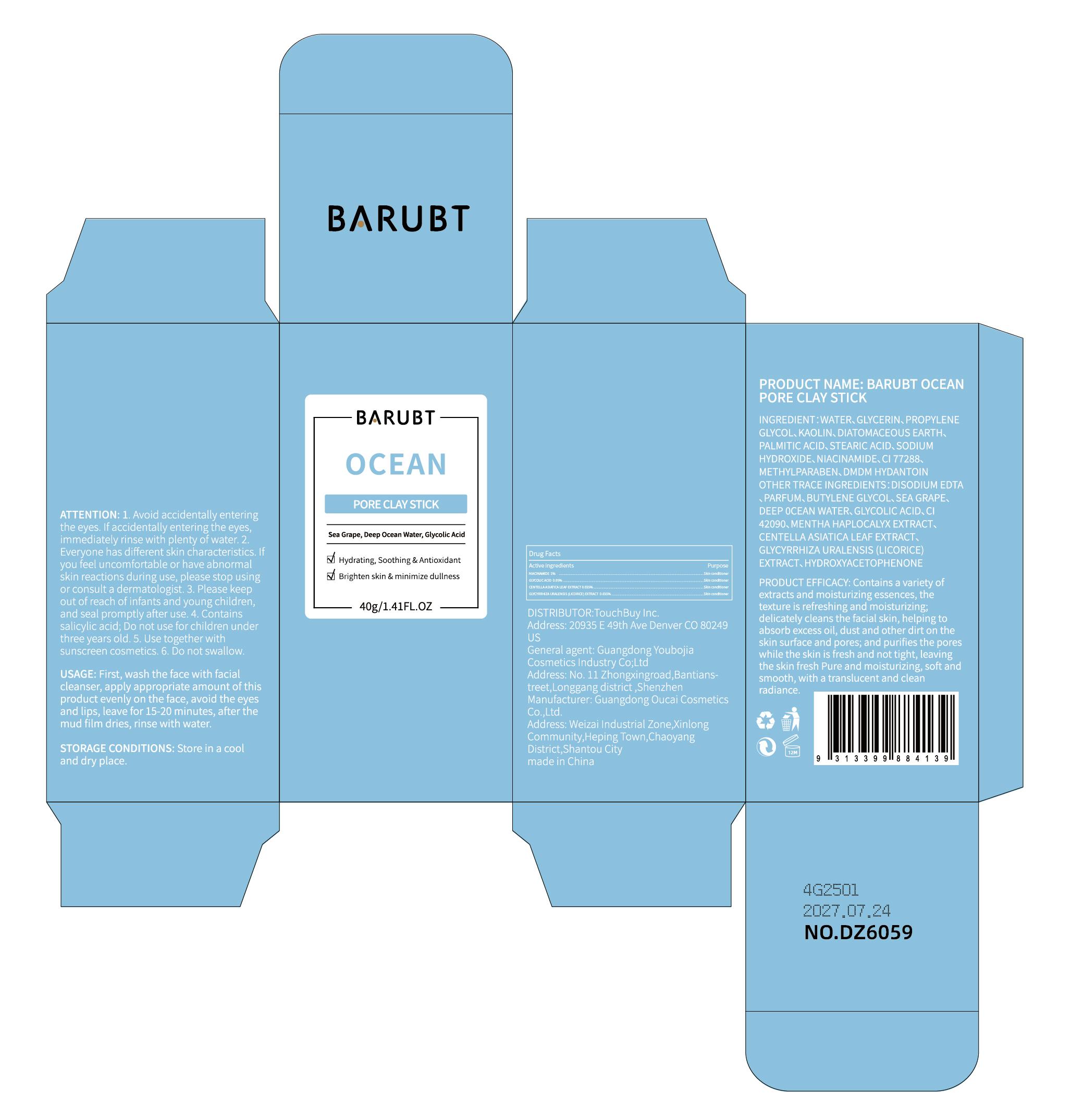 DRUG LABEL: BARUBT Ocean Pore Clay Stick
NDC: 84712-019 | Form: PASTE
Manufacturer: Guangdong Youbaijia Cosmetic Industry Co., Ltd
Category: otc | Type: HUMAN OTC DRUG LABEL
Date: 20240918

ACTIVE INGREDIENTS: CENTELLA ASIATICA LEAF 0.014 g/40 g; NIACINAMIDE 0.4 g/40 g; GLYCYRRHIZA URALENSIS 0.014 g/40 g; GLYCOLIC ACID 0.02 g/40 g
INACTIVE INGREDIENTS: STEARIC ACID 1.6 g/40 g; PALMITIC ACID 2.4 g/40 g

ACTIVE INGREDIENT

NIACINAMIDE 1%
CENTELLA ASIATICA LEAF EXTRACT 0.035%
GLYCYRRHIZA URALENSIS (LICORICE) EXTRACT 0.035%
GLYCOLIC ACID 0.05%

INACTIVE INGREDIENT

WATER
GLYCERIN
PROPYLENE GLYCOL
KAOLIN
DIATQMACEOUS EARTH
PALMITIC ACID
STEARIC ACID
SODIUM HYBROXIDE
CI 77288
METHYLPARABEN
DMDM HYDANTOIN
DISODIUM EDTA
PARFUM
BUTYLENE GLYCOL
SEA GRAPE
DEEP OCEAN WATER
CI42090
MENTHA HAPLOCALYX EXTRACT
HYDROXVACETOPHENONE

Do not use on damaged skin.

Keep away from children. Do not swallow.

PURPOSE

moisturizing and cleaning

QUESTIONS

Contact name: Jessie Peng
Company phone number: +1 818 579 7288
Company e-mail: jessie@registeragentllc.com

STOP USE

lf you feel uncomfortable or have abnormal skin reactions during use, please stop using or consult a dermatologist.

WHEN USING

keep out of eyes. Rinse with water to remove.

WARNINGS

For external use only.

STORAGE AND HANDLING

Keep away from light and in a dry place.

INDICATIONS AND USAGE

Contains a variety of extracts and moisturizing essences, the texture is refreshing and moisturizing;delicately cleans the facial skin,helping to absorb excess oil, dust and other dirt on the skin surface and pores; and purifies the pores while the skin is fresh and not tight, leaving the skin fresh Pure and moisturizing, soft and smooth, with a translucent and clean radiance

DOSAGE AND ADMINISTRATION

First, wash the face with facial cleanser, apply appropriate amount of this product evenly on the face, avoid the eyes and lips, leave for 15-20 minutes, after the mud film dries, rinse with water.